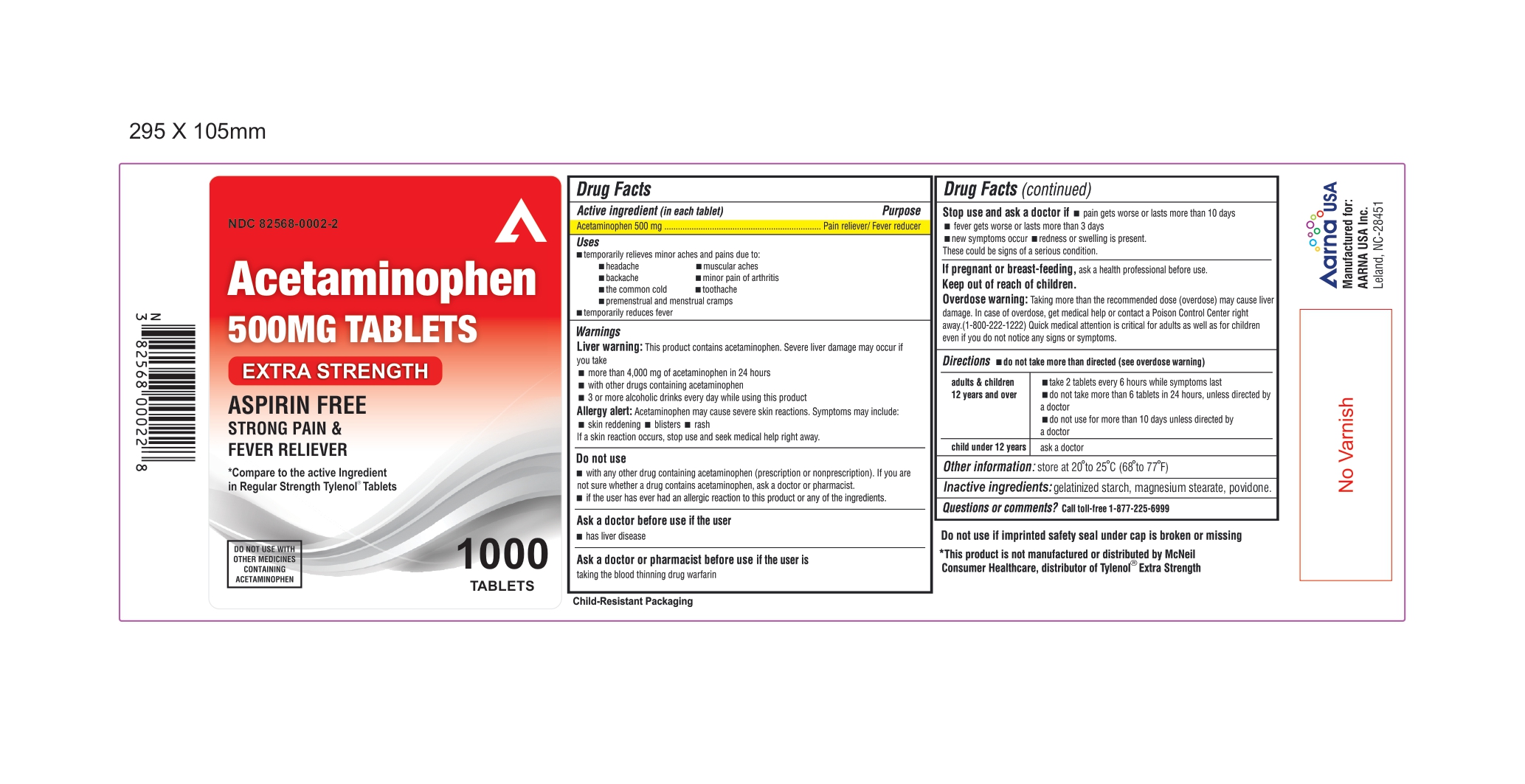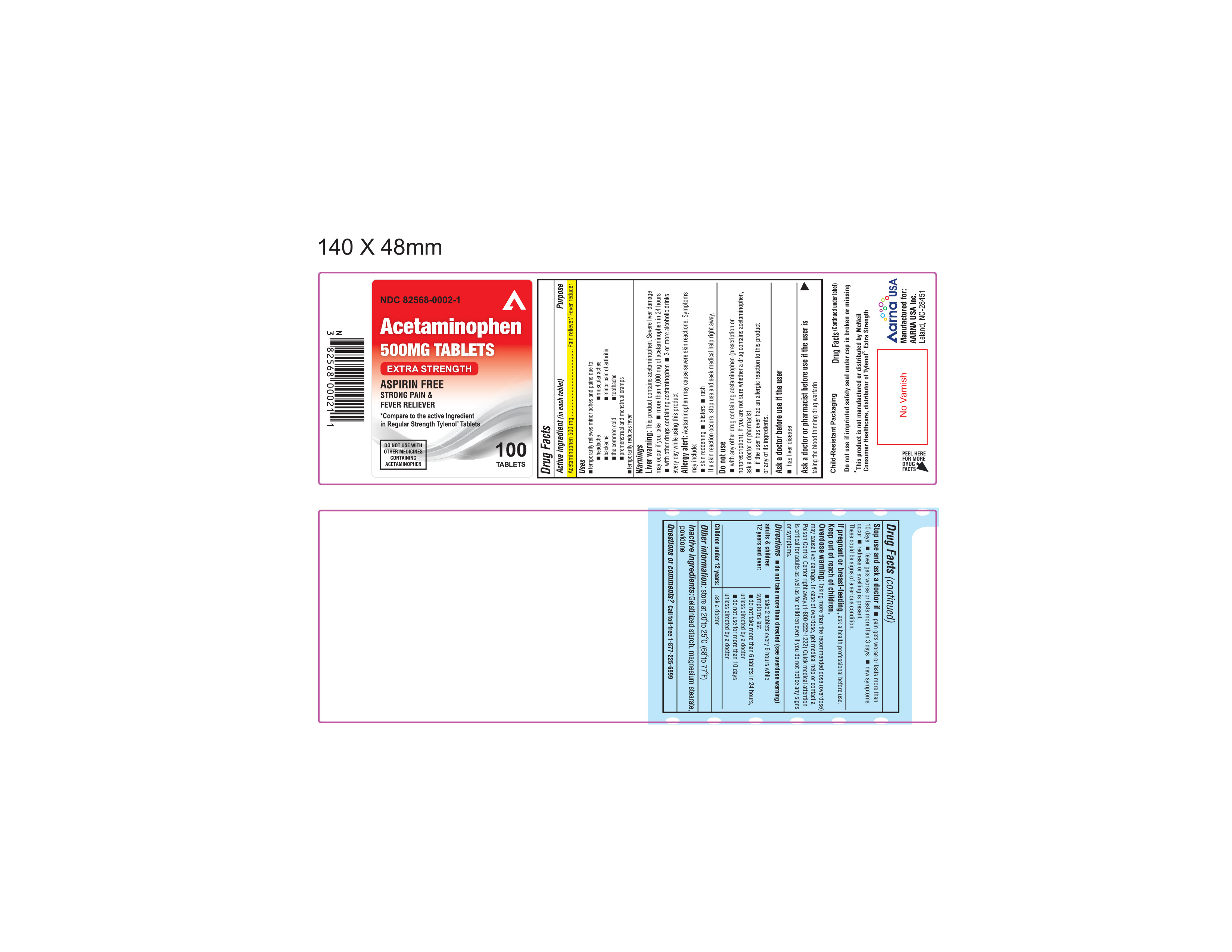 DRUG LABEL: ACETAMINOPHEN
NDC: 82568-0002 | Form: TABLET
Manufacturer: AARNA USA INC.
Category: otc | Type: HUMAN OTC DRUG LABEL
Date: 20250501

ACTIVE INGREDIENTS: ACETAMINOPHEN 500 mg/1 1
INACTIVE INGREDIENTS: MAGNESIUM STEARATE; STARCH, CORN; POVIDONE

ACTIVE INGREDIENT (IN EACH TABLET)

Acetaminophen 500 mg

PURPOSE

Pain Reliever/Fever Reducer

USES

To reduce fever and for the temporary relief of minor aches and pains due to:

•headache

•muscular aches

•backache

•minor pain of arthritis

•the common cold

•toothache

•premenstrual and menstrual cramps.

•Temporarily reduces fever.

WARNINGS

Liver warning:

This product contains acetaminophen. Severe liver damage may occur if you take

- more than 4,000 mg of acetaminophen in 24 hours
- other drugs containing acetaminophen
- 3 or more alcoholic drinks every day while using this product

Allergy alert: Acetaminophen may cause severe skin reactions. Symptoms may include:

- skin reddening
- blisters
- rash

If a skin reaction occurs, stop use and seek medical help right away.

Do not use

- with any other drug containing acetaminophen (prescription or non-prescription). If you are not sure whether a drug contains acetaminophen, ask a doctor or pharmacist.
- if the user has ever had an allergic reaction to this product or any of its ingredients.

Ask a doctor before use if the user has

has liver disease

Ask a doctor or pharmacist before use if the user is taking the blood thinning drug warfarin

Stop use and ask a doctor if:

- pain gets worse or lasts more than 10 days
- fever gets worse or lasts more than 3 days
- new symptoms occur
- redness or swelling is present.

These could be signs of a serious condition.

If pregnant or breast-feeding, ask a health professional before use.

Keep out of reach of children.

Overdose Warning:

Taking more than the recommended dose (overdose) may cause liver damage. In case of overdose, get medical help or contact a Poison Control Center right away.(1-800-222-1222)

Quick medical attention is critical for adults as well as for children even if you do not notice any signs or symptoms.

DIRECTIONS - DO NOT TAKE MORE THAN DIRECTED (SEE OVERDOSE WARNING)

adults & children 12 years and over | - take 2 tablets every 6 hours while symptoms last - do not take more than 6 tablets in 24 hours, unless directed by a doctor - do not use for more than 10 days unless directed by a doctor
children under 12 years | - ask a doctor

OTHER INFORMATION

store at 20° to 25°C (68° to 77°F)

INACTIVE INGREDIENTS:

Gelatinized starch, magnesium stearate, povidone

QUESTIONS OR COMMENTS?

Call toll-free 1-877-225-6999

Manufactured for

AARNA USA INC.

Leland, NC 28451

* This product is not manufactured or distributed by Johnson and Johnson, consumer inc., distributor of regular Tylenol Tablets.